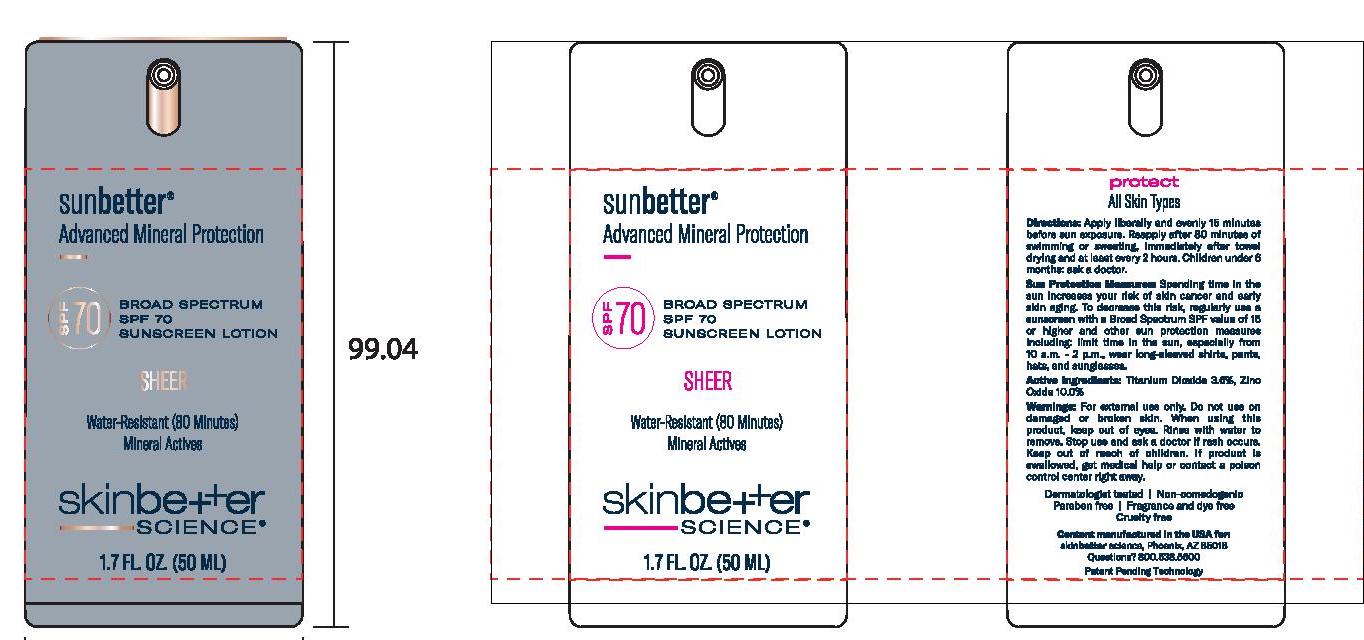 DRUG LABEL: sunbetter Broad Spectrum SPF 70 Sunscreen Sheer
NDC: 73291-0004 | Form: LOTION
Manufacturer: SKINBETTER SCIENCE LLC
Category: otc | Type: HUMAN OTC DRUG LABEL
Date: 20250106

ACTIVE INGREDIENTS: ZINC OXIDE 100 mg/1 mL; TITANIUM DIOXIDE 36 mg/1 mL
INACTIVE INGREDIENTS: MAGNESIUM POTASSIUM ALUMINOSILICATE FLUORIDE; NIACINAMIDE; BUTYLOCTYL SALICYLATE; POLYGLYCERYL-4 OLEATE; 1,2-HEXANEDIOL; ALUMINUM OXIDE; HIMANTHALIA ELONGATA; PHENYLETHYL ALCOHOL; CERIC OXIDE; .ALPHA.-TOCOPHEROL ACETATE, DL-; STEARIC ACID; WATER; DIMETHICONE; CETYL DIMETHICONE 45; SILICON DIOXIDE; CAPRYLYL GLYCOL; DISTEARDIMONIUM HECTORITE; POLY(METHYL METHACRYLATE; 450000 MW); DODECAMETHYLPENTASILOXANE; POLYHYDROXYSTEARIC ACID (2300 MW); STYRENE/ACRYLAMIDE COPOLYMER (500000 MW); MEDIUM-CHAIN TRIGLYCERIDES; SQUALANE; PHENYL TRIMETHICONE; GLYCERIN; SODIUM CHLORIDE; TRIETHYL CITRATE; .ALPHA.-BISABOLOL, (+/-)-; PANTHENOL

sunbetter SHEER SPF 70 Sunscreen Lotion

Drug Facts

Active ingredients

Titanium Dioxide 3.6%

Zinc Oxide 10.0%

Purpose

Sunscreen

Uses

- Helps prevent sunburn.
- If used as directed with other sun protection measures (see Directions), decreases the risk of skin cancer and early skin aging caused by the sun.

Warnings

For external use only.

Do not use on damaged or broken skin.

When using this product keep out of eyes. Rinse with water to remove.

Stop use and ask a doctor if rash occurs.

Keep out of reach of children. If swallowed, get medical help or contact a Poison Control Center right away.

Directions

Sun Protection Measures: Spending time in the sun increases your risk of skin cancer and early skin aging. To decrease this risk, regularly use a sunscreen with a Broad Spectrum SPF value of 15 or higher and other sun protection measures including:

limit time in the sun, especially from 10 a.m. - 2 p.m.

wear long-sleeved shirts, pants, hats and sunglasses.

Children under 6 months of age: Ask a doctor.

DOSAGE AND ADMINISTRATION

Apply liberally and evenly 15 minutes before sun exposure.

Reapply:

after 80 minutes of swimming or sweating.

immediately after towel drying.

at least every 2 hours.

use a water resistant sunscreen if swimming or sweating.

Inactive ingredients

1,2-Hexanediol, Acrylates/Dimethicone Copolymer, Allantoin, Alumina, Bis-Vinyl Dimethicone/Dimethicone Copolymer, Bisabolol, Butyloctyl Salicylate, Camellia Oleifera Leaf Extract, Capparis Spinosa Fruit Extract, Caprylic/Capric Triglyceride, Caprylyl Glycol, Cerium Oxide, Cetyl Dimethicone, Dimethicone, Disteardimonium Hectorite, Glycerin, Himanthalia Elongata Extract, Niacinamide, Olea Europaea (Olive) Fruit Extract, Olea Europaea (Olive) Leaf Extract, Opuntia Ficus-Indica Stem Extract, Panthenol, Phenethyl Alcohol, Phenoxyethanol, Phenyl Trimethicone, Plankton Extract, Polyglyceryl-3 Sorbityl Linseedate, Polyglyceryl-4 Oleate, Polygonum Aviculare Extract, Polyhydroxystearic Acid, Polymethyl Methacrylate, Potassium Sorbate, Silica, Sodium Benzoate, Sodium Chloride, Squalane, Stearic Acid, Styrene/Acrylates Copolymer, Synthetic Fluorphlogopite, Tocopheryl Acetate, Triethyl Citrate, Tropolone, Ubiquinone, Water, Zea Mays (Corn) Starch, Zingiber Officinale (Ginger) Root Extract.

Other information

Protect this product from excessive heat and direct sun.

Questions or comments?

800-538-5600

Principal Display Panel

sunbetter™

Advanced Mineral Protection

BROAD SPECTRUM SPF 70

SUNSCREEN LOTION

SHEER

Water-Resistant (80 Minutes)

Mineral Actives

skinbetter science®

1.7 FL.OZ. (50 ML)